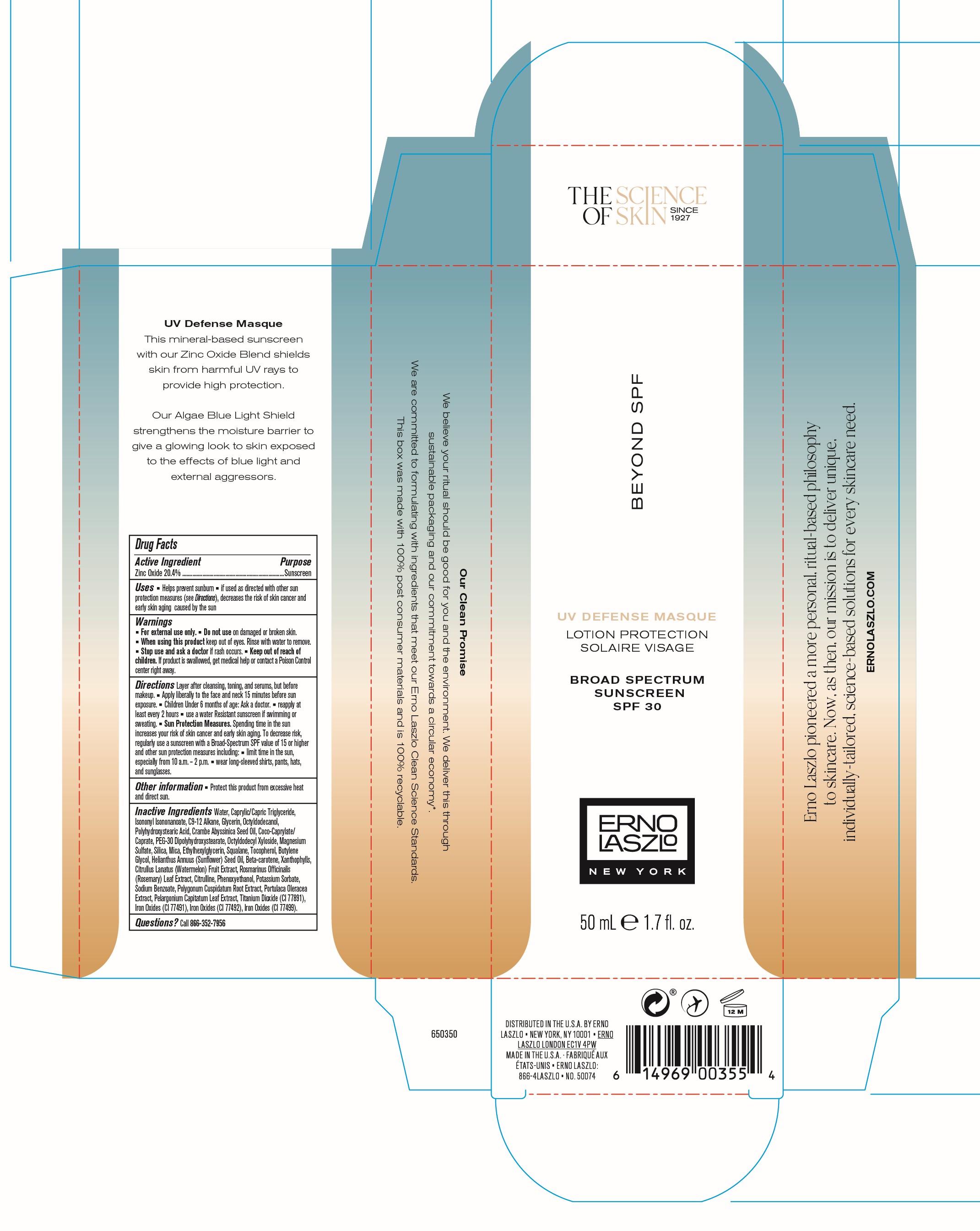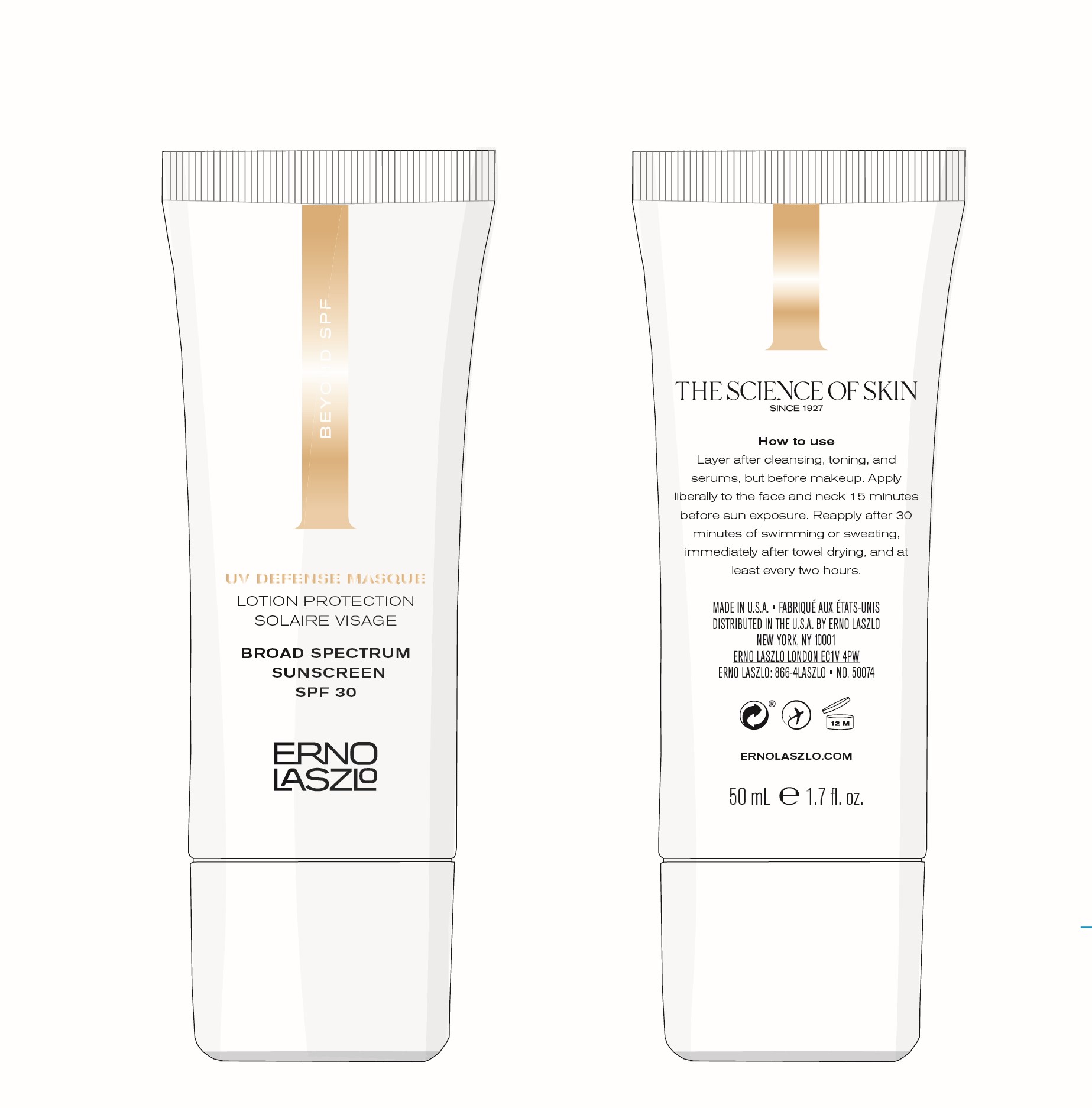 DRUG LABEL: Beyond SPF UV Defense Masque SPF 30
NDC: 57913-2804 | Form: LOTION
Manufacturer: Erno Laszlo, Inc.
Category: otc | Type: HUMAN OTC DRUG LABEL
Date: 20241015

ACTIVE INGREDIENTS: ZINC OXIDE 20.4 g/100 mL
INACTIVE INGREDIENTS: SILICON DIOXIDE; POLYGONUM CUSPIDATUM ROOT; WATER; BETA CAROTENE; OCTYLDODECYL XYLOSIDE; ETHYLHEXYLGLYCERIN; CRAMBE HISPANICA SUBSP. ABYSSINICA SEED OIL; MICA; ROSMARINUS OFFICINALIS WHOLE; PORTULACA OLERACEA WHOLE; PELARGONIUM CAPITATUM LEAF; FERRIC OXIDE YELLOW; FERROSOFERRIC OXIDE; MAGNESIUM SULFATE, UNSPECIFIED; HELIANTHUS ANNUUS FLOWERING TOP; FERRIC OXIDE RED; TITANIUM DIOXIDE; SODIUM BENZOATE; OCTYLDODECANOL; CITRULLINE; PHENOXYETHANOL; POTASSIUM SORBATE; SQUALANE; POLYHYDROXYSTEARIC ACID (2300 MW); PEG-30 DIPOLYHYDROXYSTEARATE; CITRULLUS LANATUS VAR. LANATUS WHOLE; CAPRYLIC/CAPRIC/LINOLEIC TRIGLYCERIDE; GLYCERIN; C18-C21 ALKANE; .ALPHA.-TOCOPHEROL, DL-; BUTYLENE GLYCOL; LUTEIN; ISONONYL ISONONANOATE; COCO-CAPRYLATE/CAPRATE

Active Ingredient Section

Zinc oxide 20.4%

Purpose

Sunscreen

Uses

Helps prevent sunburn ▪ if used as directed with other sun protection measures (see Directions), decreases the risk of skin cancer and early skin aging caused by the sun

Warnings

For external use only. ▪ Do not use on damaged or broken skin. ▪ When using this product keep out of eyes. Rinse with water to remove. ▪ Stop use and ask a doctor if rash occurs. ▪ Keep out of reach of children. If product is swallowed, get medical help or contact a Poison Control center right away.

Keep out of reach of children.

Directions

Layer after cleansing, toning, and serums, but before makeup. ▪ Apply liberally to the face and neck 15 minutes before sun exposure. ▪ Children Under 6 months of age: Ask a doctor. ▪ reapply at least every 2 hours ▪ use a water Resistant sunscreen if swimming or sweating. ▪ Sun Protection Measures. Spending time in the sun increases your risk of skin cancer and early skin aging. To decrease risk, regularly use a sunscreen with a Broad-Spectrum SPF value of 15 or higher and other sun protection measures including: ▪ limit time in the sun, especially from 10 a.m. – 2 p.m. ▪ wear long-sleeved shirts, pants, hats, and sunglasses.

Other Information

Protect this product from excessive heat and direct sun.

Inactive Ingredients

Water, Caprylic/Capric Triglyceride, Isononyl Isononanoate, C9-12 Alkane, Glycerin, Octyldodecanol, Polyhydroxystearic Acid, Crambe Abyssinica Seed Oil, Coco-Caprylate/Caprate, PEG-30 Dipolyhydroxystearate, Octyldodecyl Xyloside, Magnesium Sulfate, Silica, Mica, Ethylhexylglycerin, Squalane, Tocopherol, Butylene Glycol, Helianthus Annuus (Sunflower) Seed Oil, Beta-carotene, Xanthophylls, Citrullus Lanatus (Watermelon) Fruit Extract, Rosmarinus Officinalis (Rosemary) Leaf Extract, Citrulline, Phenoxyethanol, Potassium Sorbate, Sodium Benzoate, Polygonum Cuspidatum Root Extract, Portulaca Oleracea Extract, Pelargonium Capitatum Leaf Extract, Titanium Dioxide (CI 77891), Iron Oxides (CI 77491), Iron Oxides (CI 77492), Iron Oxides (CI 77499).

Questions?

Call 866-452-7956